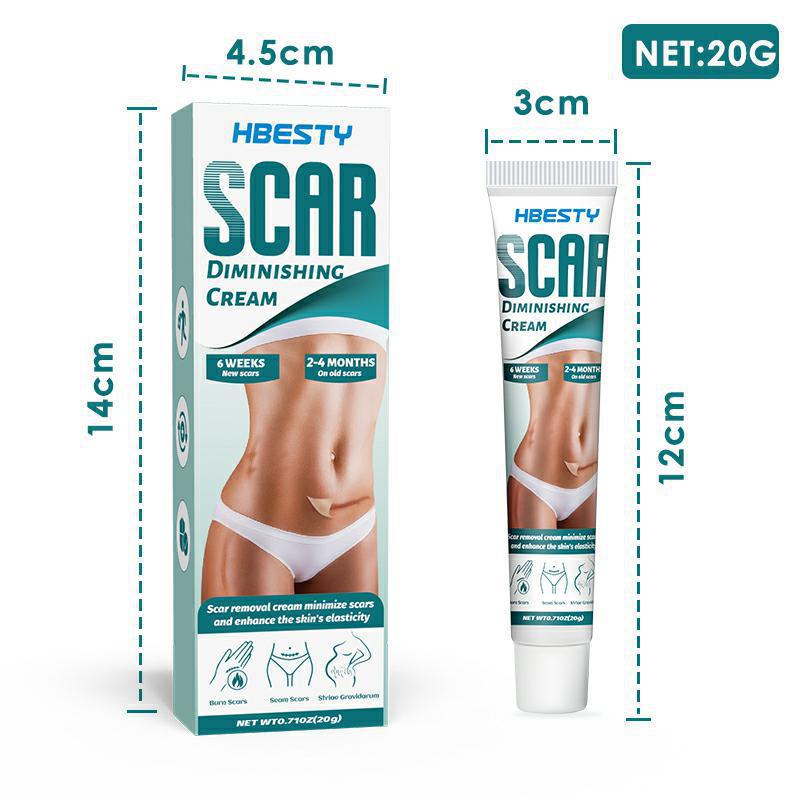 DRUG LABEL: Scar Diminishing Cream
NDC: 83675-018 | Form: CREAM
Manufacturer: Guangzhou Hanhai Trading Co., Ltd
Category: otc | Type: HUMAN OTC DRUG LABEL
Date: 20231007

ACTIVE INGREDIENTS: CAMPHOR (NATURAL) 13 g/100 g
INACTIVE INGREDIENTS: ARCHANGELENONE; MINT

Active Ingredient

Camphor 13.0%

Purpose

Scar Diminishing

Use

scar removat aram mihimie soar
and mhomce the shin's clasticity

Warnings

For external use only. Do not take it internally.

Keep Out Of Reach Of Children
Sensitive Skin

Do not use

Product shall not be eat

When Using

After cleaning the abdomen .take appropriate gel evenlyon the abdomen

Stop Use

In case of adverse reactions, please stop using this product.If the symptoms.

Ask Doctor

ask doctor in case of Sensitive Skin

Keep Oot Of Reach Of Children

Keep Out Of Reach Of Children

Directions

After cleaning the abdomen .take appropriate gel evenlyon the abdomen

Other information

Store the product in a cool, dry and well-ventilated place

Avoid direct sunlight

Inactive ingredients

Silicone

Mint